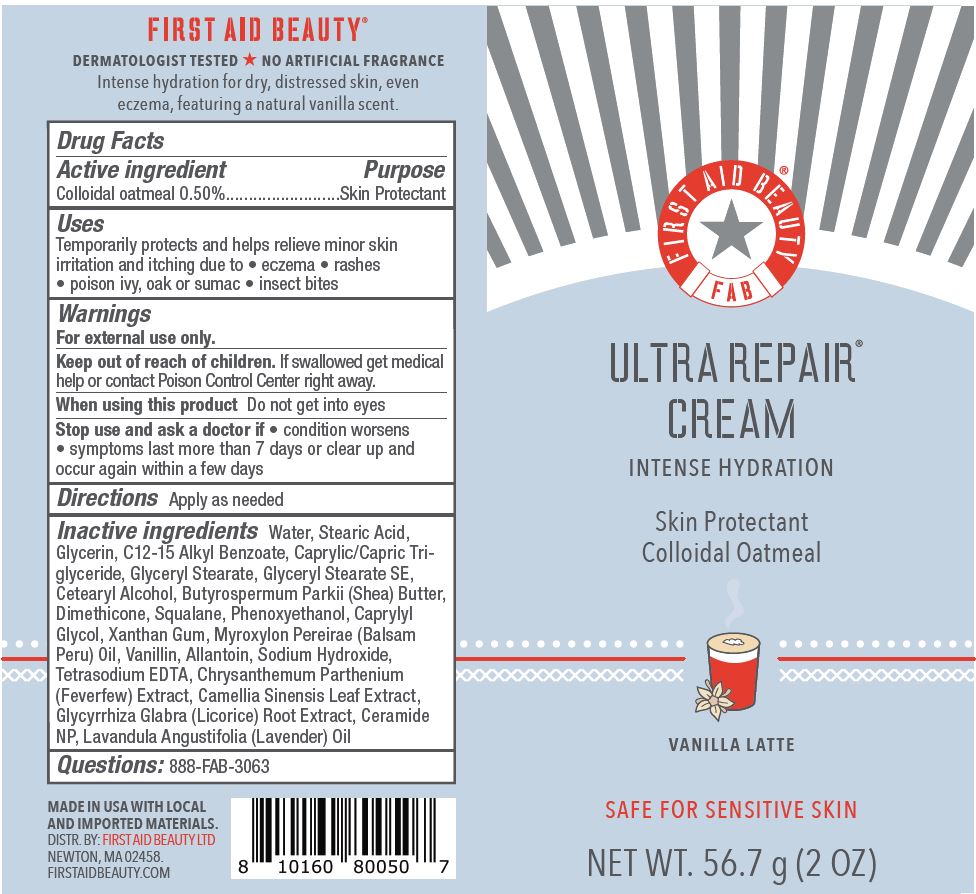 DRUG LABEL: First Aid Beauty FAB Ultra Repair Skin Protectant Vanilla Latte
NDC: 84126-047 | Form: CREAM
Manufacturer: The Procter & Gamble Manufacturing Company
Category: otc | Type: HUMAN OTC DRUG LABEL
Date: 20251231

ACTIVE INGREDIENTS: OATMEAL 0.5 g/100 g
INACTIVE INGREDIENTS: VANILLIN; CETEARYL ALCOHOL; SQUALANE; DIMETHICONE; TETRASODIUM EDTA; GLYCERYL STEARATE SE; C12-15 ALKYL BENZOATE; CAMELLIA SINENSIS LEAF; CAPRYLYL GLYCOL; SODIUM HYDROXIDE; PHENOXYETHANOL; BUTYROSPERMUM PARKII (SHEA) BUTTER; GLYCYRRHIZA GLABRA (LICORICE) ROOT; WATER; GLYCERIN; ALLANTOIN; GLYCERYL STEARATE; CAPRYLIC/CAPRIC TRIGLYCERIDE; STEARIC ACID; XANTHAN GUM; CERAMIDE NP; TANACETUM PARTHENIUM WHOLE; MYROXYLON PEREIRAE (BALSAM PERU) OIL; MENTHA AQUATICA VAR. CITRATA LEAF; LAVANDULA ANGUSTIFOLIA (LAVENDER) OIL

First Aid Beauty FAB Ultra Repair Cream Skin Protectant Vanilla Latte

Drug Facts

Active ingredients

Colloidal Oatmeal 0.5%

Purpose

Skin Protectant

Uses

- Temporarily protects and helps relieve minor skin irritation and itching due to eczema, rashes, poison ivy, oak or sumac, insect bites

Warnings

For external use only.

Keep out of reach of children. If swallowed, get medical help or contact a Poison Control Center right away.

WHEN USING

Do not get into eyes.

Stop use and ask a doctor if condition worsens, symptoms last more than 7 days or clear up and occur again within a few days

Directions

Apply as needed

INACTIVE INGREDIENT

Water, Stearic Acid, Glycerin, C12-15 Alkyl Benzoate, Caprylic/Capric Triglyceride, Glyceryl Stearate, Glyceryl Stearate SE, Cetearyl Alcohol, Butyrospermum Parkii (Shea) Butter, Dimethicone, Squalane, Phenoxyethanol, Caprylyl Glycol, Xanthan Gum, Myroxylon Pereirae (Balsam Peru) Oil, Vanillin, Allantoin, Sodium Hydroxide, Tetrasodium EDTA, Chrysanthemum Parthenium (Feverfew) Extract, Camellia Sinensis Leaf Extract, Glycyrrhiza Glabra (Licorice) Root Extract, Ceramide NP, Lavandula Angustifolia (Lavender) Oil

Questions:

888-FAB-3063

MADE IN USA

FIRST AID BEAUTY LTD

NEWTON, MA 02458

WWW.FIRSTAIDBEAUTY.COM

PRINCIPAL DISPLAY PANEL - 56.7 g (2 oz)

First Aid Beauty

FAB

Ultra Repair® Cream

Intense Hydration

Vanilla Latte

Skin Protectant Colloidal Oatmeal

Net Wt. 56.7 g (2 oz)